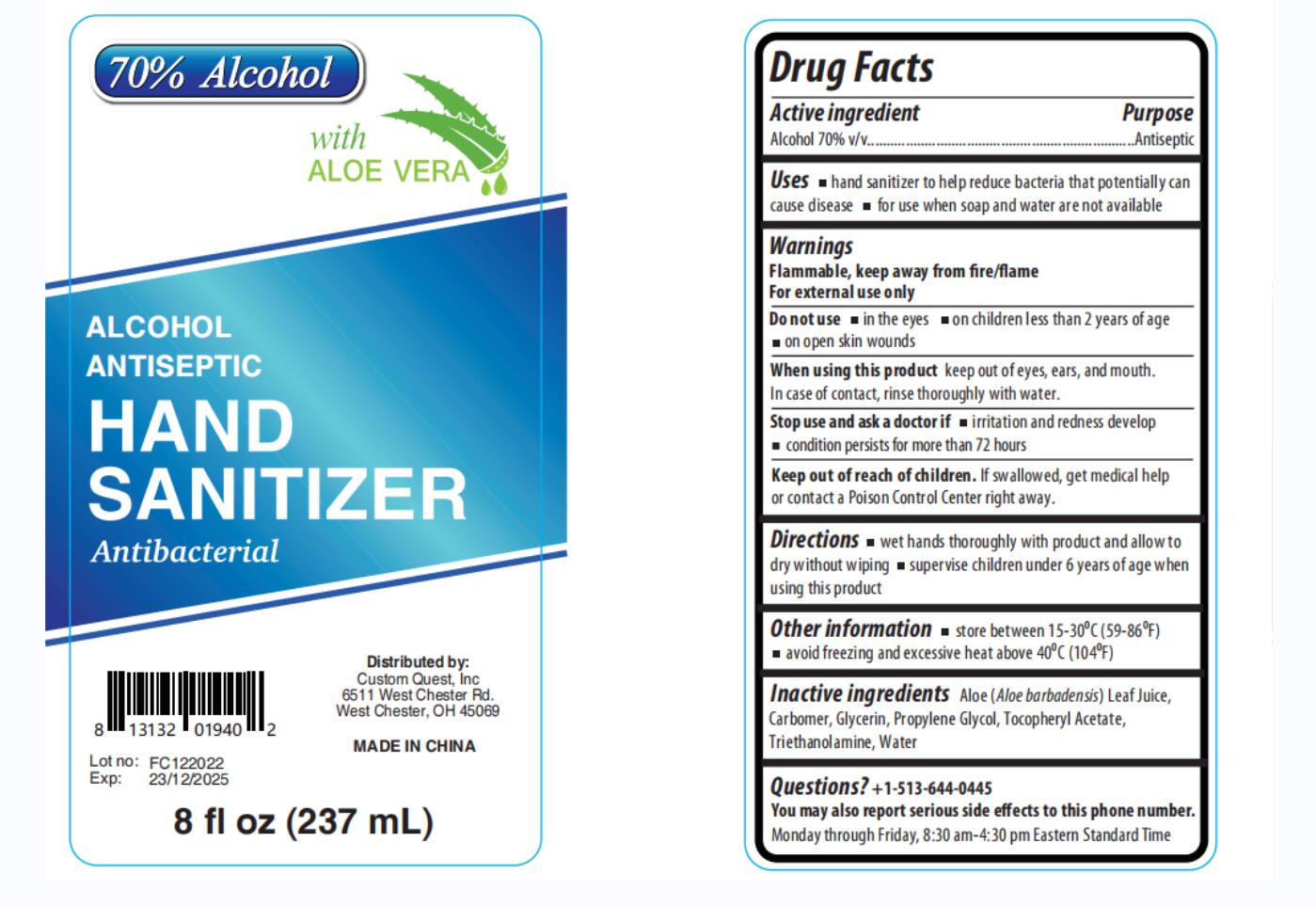 DRUG LABEL: Hand Sanitizer
NDC: 43116-030 | Form: LIQUID
Manufacturer: Shenzhen Shierjie Biological Engineering Co., LTD
Category: otc | Type: HUMAN OTC DRUG LABEL
Date: 20221206

ACTIVE INGREDIENTS: ALCOHOL 70 mL/100 mL
INACTIVE INGREDIENTS: WATER; TROLAMINE; CARBOMER HOMOPOLYMER, UNSPECIFIED TYPE; GLYCERIN; ALPHA-TOCOPHEROL ACETATE; ALOE VERA LEAF; PROPYLENE GLYCOL

43116-030
Hand Sanitizer

Active Ingredient

Ethyl Alcohol 75%

Purpose

Antiseptic

Uses

- hand sanitizer to help reduce bacteria that potentially can cause disease

- for use when soap and water are not available

Warnings

Flammable, keep away from fire/flame

For external use only

Do not use

- in the eyes

- on children less than 2 years of age

- on open skin wounds

When using this product

keep out of eyes, ears, and mouth. In case of contact, rinse thoroughly with water.

Stop use and ask a doctor if

- irritation and redness develop
- condition persists for more than 72 hours

Keep out of reach of children

If swallowed, get medical help or contact a Poison Control Center right away.

Directions

wet hands thoroughly with product and allow to dry without wiping

supervise children under 6 years of age when using this product

Other information

- Other information a store between 15-30°C (59-86F)

- avoid freeing and excessive heat above 40°C (104F)

Inactive ingredients

Aloe (Aloe barbadensis) Leaf Juice, Carbomer , Glycerin , Propylene Glycol , Tocopheryl Acetate ,Triethanolamine , Water